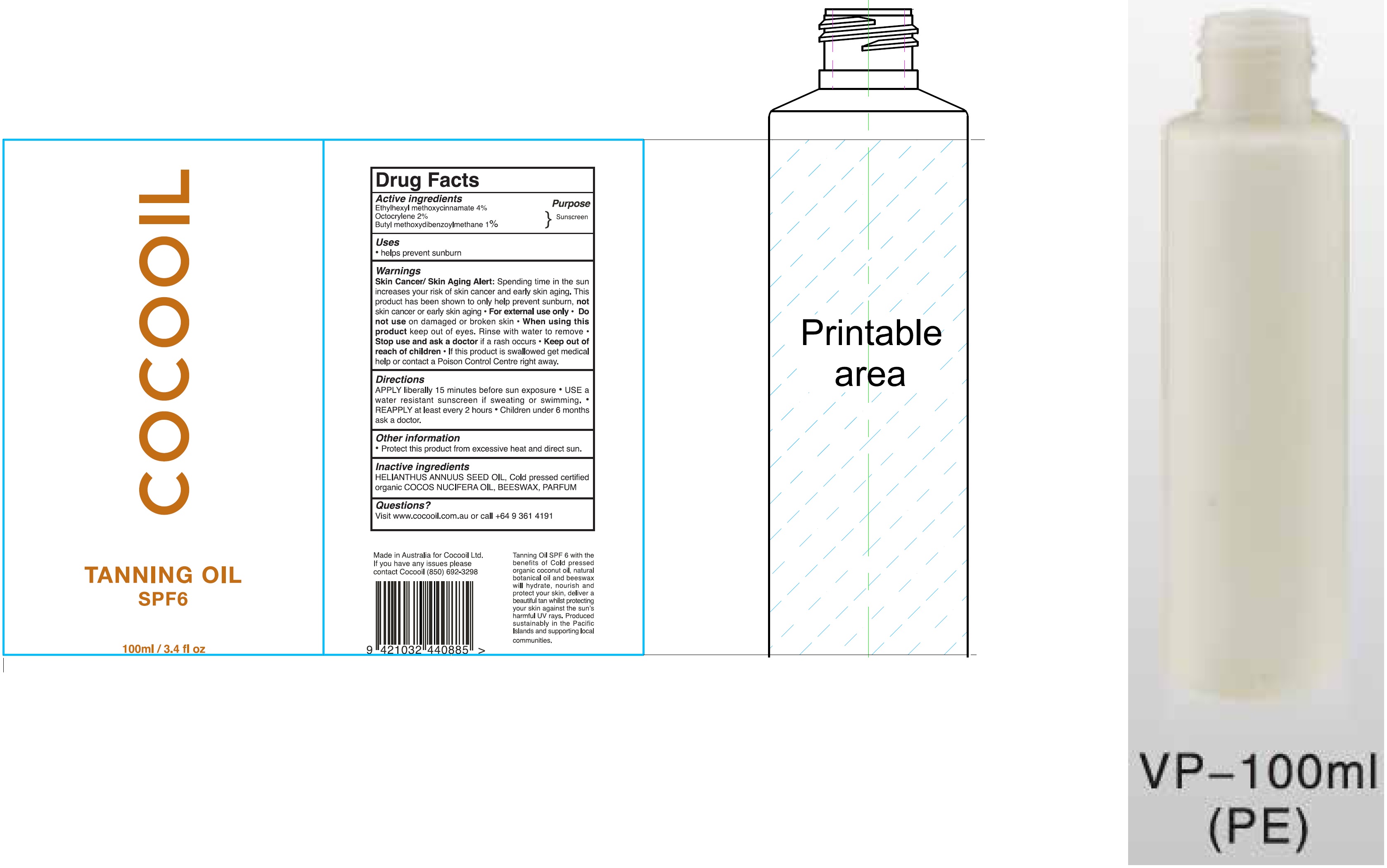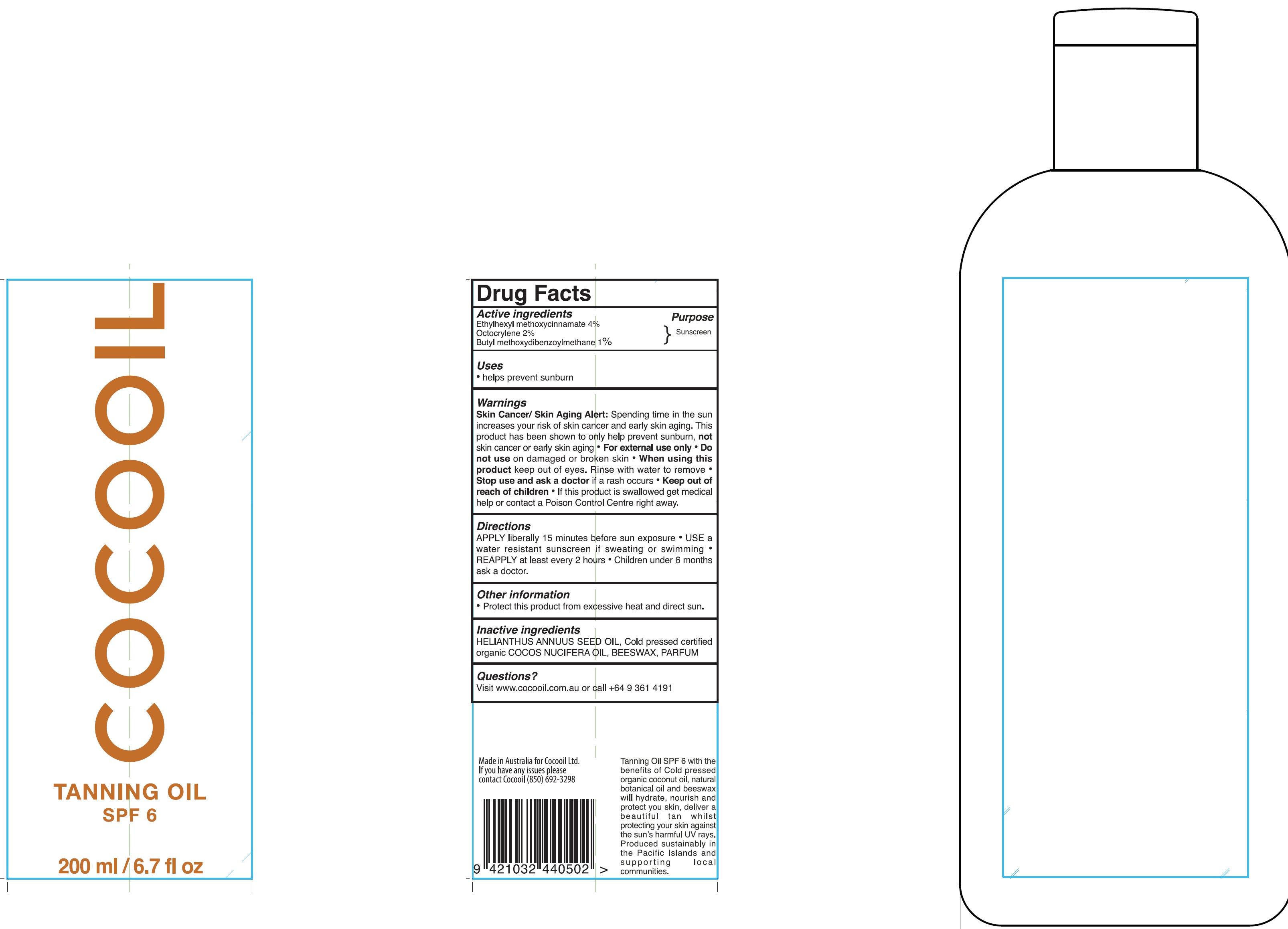 DRUG LABEL: COCOOIL SPF 6
NDC: 72645-004 | Form: LOTION
Manufacturer: Cocooil Limited
Category: otc | Type: HUMAN OTC DRUG LABEL
Date: 20200904

ACTIVE INGREDIENTS: OCTINOXATE 40 mg/1 mL; OCTOCRYLENE 20 mg/1 mL; AVOBENZONE 10 mg/1 mL
INACTIVE INGREDIENTS: SUNFLOWER OIL; YELLOW WAX

COCOOIL SPF 6 Bottle

Active ingredients

Ethylhexyl methoxycinnamate 4%
Octocrylene 2%
Butyl methoxydibenzoylmethane 1%

Purpose

Sunscreen

Uses

- helps prevent sunburn

Warnings

Skin Cancer/ Skin Aging Alert: Spending time in the sun increases your risk of skin cancer and early skin aging. This product has been shown to only help prevent sunburn, not skin cancer or early skin aging

- For external use only

Do not use

- on damaged or broken skin

When using this product

- keep out of eyes. Rinse with water to remove

Stop use and ask a doctor

if a rash occurs

Keep out of reach of children

- If this product is swallowed get medical help or contact a Poison Control Center right away.

Directions

APPLY liberally 15 minutes before sun exposure

- USE a water resistant sunscreen if sweating or swimming.
- REAPPLY at least every 2 hours
- Children under 6 months ask a doctor.

Other information

- Protect this product from excessive heat and direct sun.

Inactive ingredients

HELIANTHUS ANNUUS SEED OIL, Cold pressed certified organic COCO NUCIFERA OIL, BEESWAX, PARFUM

Questions?

Visit www.cocooil.com.au or call +6493614191